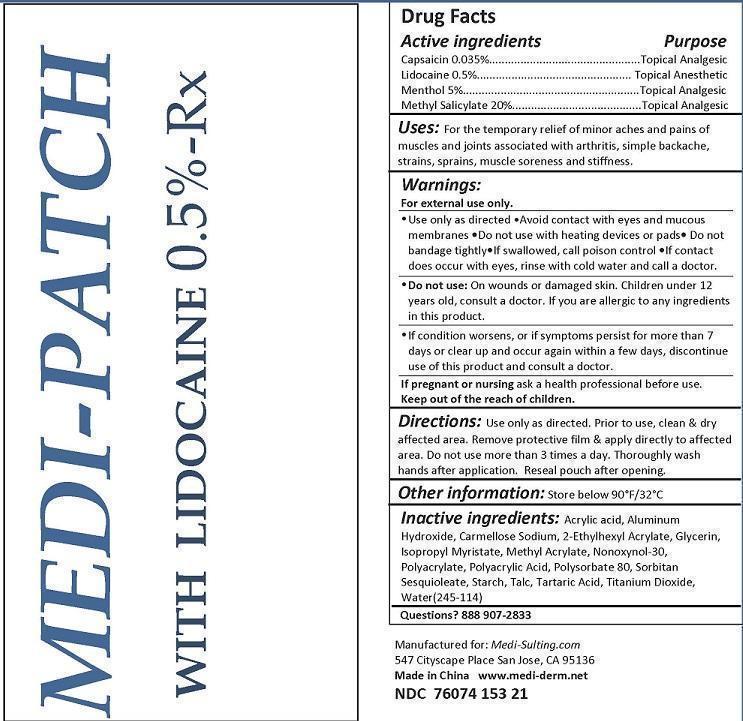 DRUG LABEL: MEDI-PATCH WITH LIDOCAINE
NDC: 76074-163 | Form: PATCH
Manufacturer: Two Hip Consulting, LLC
Category: prescription | Type: HUMAN PRESCRIPTION DRUG LABEL
Date: 20160714

ACTIVE INGREDIENTS: METHYL SALICYLATE 10 g/1 1; MENTHOL 2.5 g/1 1; CAPSAICIN 0.0175 g/1 1; LIDOCAINE 0.25 g/1 1
INACTIVE INGREDIENTS: ACRYLIC ACID; ALUMINUM HYDROXIDE; CROSCARMELLOSE SODIUM; ETHYLHEXYL ACETATE; GLYCERIN; ISOPROPYL MYRISTATE; METHYL ACRYLATE; NONOXYNOL-30; SODIUM POLYACRYLATE (2500000 MW); POLYACRYLIC ACID (800000 MW); POLYSORBATE 80; SORBITAN SESQUIOLEATE; STARCH, CORN; TALC; TARTARIC ACID; TITANIUM DIOXIDE; WATER

INDICATIONS AND USAGE

USES: FOR THE TEMPORARY RELIEF OF MINOR ACHES AND PAINS OF MUSCLES AND JOINTS ASSOCIATED WITH ARTHRITIS, SIMPLE BACKACHE, STRAINS, SPRAINS, MUSCLE SORENESS AND STIFFNESS.

DIRECTIONS:

USE AS DIRECTED. PRIOR TO USE, CLEAN AND DRY AFFECTED AREA. REMOVE PROTECTIVE FILM AND APPLY DIRECTLY TO AFFECTED AREA. DO NOT USE MORE THAN 3 TIMES A DAY. THOROUGHLY WASH HANDS AFTER APPLICATION. RESEAL POUCH AFTER OPENING.

INACTIVE INGREDIENT

Inactive Ingredients: ACRLIC ACID, ALUMINUM HYDROXIDE, CARMELLOSE SODIEM, 2-ETHYLHEXYL ACRYLATE, GLYCERIN, ISOPROPYL MYRISTATE, METHYL ACRYLATE, NONOXYNOL-30, POLYACRYLATE, POLYACRYLIC ACID, POLYSORBATE 80, SORBITAN SESQUIOLEATE, STARCH, TALC, TARTARIC ACID, TITANIUM DIOXIDE, WATER.

OTHER INFORMATION: STORE BELOW 90°F/32°C

PREGNANCY

IF PREGNANT OR NURSING ASK A HEALTH PROFESSIONAL BEFORE USE.

WARNINGS

Warnings: For external use only. Use only as directed. Avoid contact with eyes and mucous membranes. Do not use with heating devices or pads. Do not cover or bandage tightly. If swallowed, call poison control. If contact does occur with eyes rinse with cold water and call a doctor.